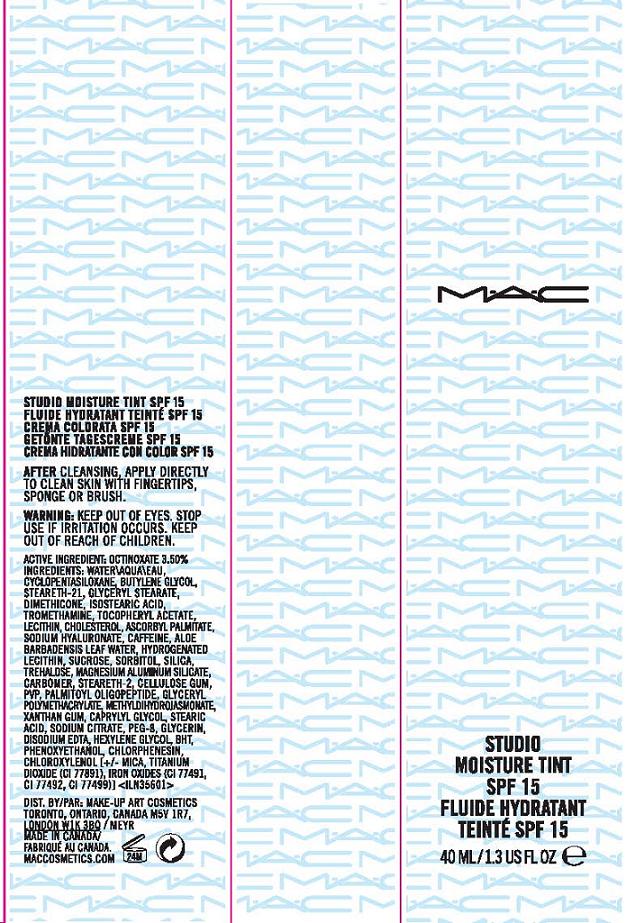 DRUG LABEL: STUDIO MOISTURE TINT
NDC: 40046-0033 | Form: GEL
Manufacturer: MAKE UP ART COSMETICS
Category: otc | Type: HUMAN OTC DRUG LABEL
Date: 20110620

ACTIVE INGREDIENTS: OCTINOXATE 3.5 mL/100 mL
INACTIVE INGREDIENTS: WATER; CYCLOMETHICONE 5; BUTYLENE GLYCOL; STEARETH-21; GLYCERYL MONOSTEARATE; DIMETHICONE; ISOSTEARIC ACID; TROMETHAMINE; .ALPHA.-TOCOPHEROL ACETATE, D-; LECITHIN, SOYBEAN; CHOLESTEROL; ASCORBYL PALMITATE; HYALURONATE SODIUM; CAFFEINE; ALOE VERA LEAF; HYDROGENATED SOYBEAN LECITHIN; SUCROSE; SORBITOL; SILICON DIOXIDE; TREHALOSE; MAGNESIUM ALUMINUM SILICATE; CARBOMER HOMOPOLYMER TYPE C; STEARETH-2; CARBOXYMETHYLCELLULOSE SODIUM; PALMITOYL OLIGOPEPTIDE; XANTHAN GUM; CAPRYLYL GLYCOL; STEARIC ACID; SODIUM CITRATE; GLYCERIN; EDETATE DISODIUM; HEXYLENE GLYCOL; BUTYLATED HYDROXYTOLUENE; PHENOXYETHANOL; CHLORPHENESIN; CHLOROXYLENOL; MICA; TITANIUM DIOXIDE; FERROSOFERRIC OXIDE; FERRIC OXIDE YELLOW; FERRIC OXIDE RED

ACTIVE INGREDIENT: OCTINOXATE, 3.5%

INACTIVE INGREDIENT

INACTIVE INGREDIENTS: WATER [] CYCLOPENTASILOXANE [] BUTYLENE GLYCOL [] STEARETH-21 [] GLYCERYL STEARATE [] DIMETHICONE [] ISOSTEARIC ACID [] TROMETHAMINE [] TOCOPHERYL ACETATE [] LECITHIN [] CHOLESTEROL [] ASCORBYL PALMITATE [] SODIUM HYALURONATE [] CAFFEINE [] ALOE BARBADENSIS LEAF WATER [] HYDROGENATED LECITHIN [] SUCROSE [] SORBITOL [] SILICA [] TREHALOSE [] MAGNESIUM ALUMINUM SILICATE [] CARBOMER [] STEARETH-2 [] CELLULOSE GUM [] PVP [] PALMITOYL OLIGOPEPTIDE [] GLYCERYL POLYMETHACRYLATE [] METHYLDIHYDROJASMONATE [] XANTHAN GUM [] CAPRYLYL GLYCOL [] STEARIC ACID [] SODIUM CITRATE [] PEG-8 [] GLYCERIN [] DISODIUM EDTA [] HEXYLENE GLYCOL [] BHT [] PHENOXYETHANOL [] CHLORPHENESIN [] CHLOROXYLENOL [] [+/- MICA [] TITANIUM DIOXIDE (CI 77891) [] IRON OXIDES (CI 77491, CI 77492, CI 77499)

WHEN USING

DIRECTIONS: AFTER CLEANSING, APPLY TO CLEAN SKIN WITH FINGERTIPS, SPONGE OR BRUSH

WARNINGS

WARNING: KEEP OUT OF EYES. STOP USE IF IRRITATION OCCURS. KEEP OUT OF REACH OF CHILDREN.

PACKAGE LABEL

PRINCIPAL DISPLAY PANEL:

MAC

STUDIO MOISTURE TINT
SPF 15
40 ML/1.3 US FL OZ
DISTR MAKE UP ART COSMETICS
TORONTO, ONTARIO, CANADA, M5V 1R7